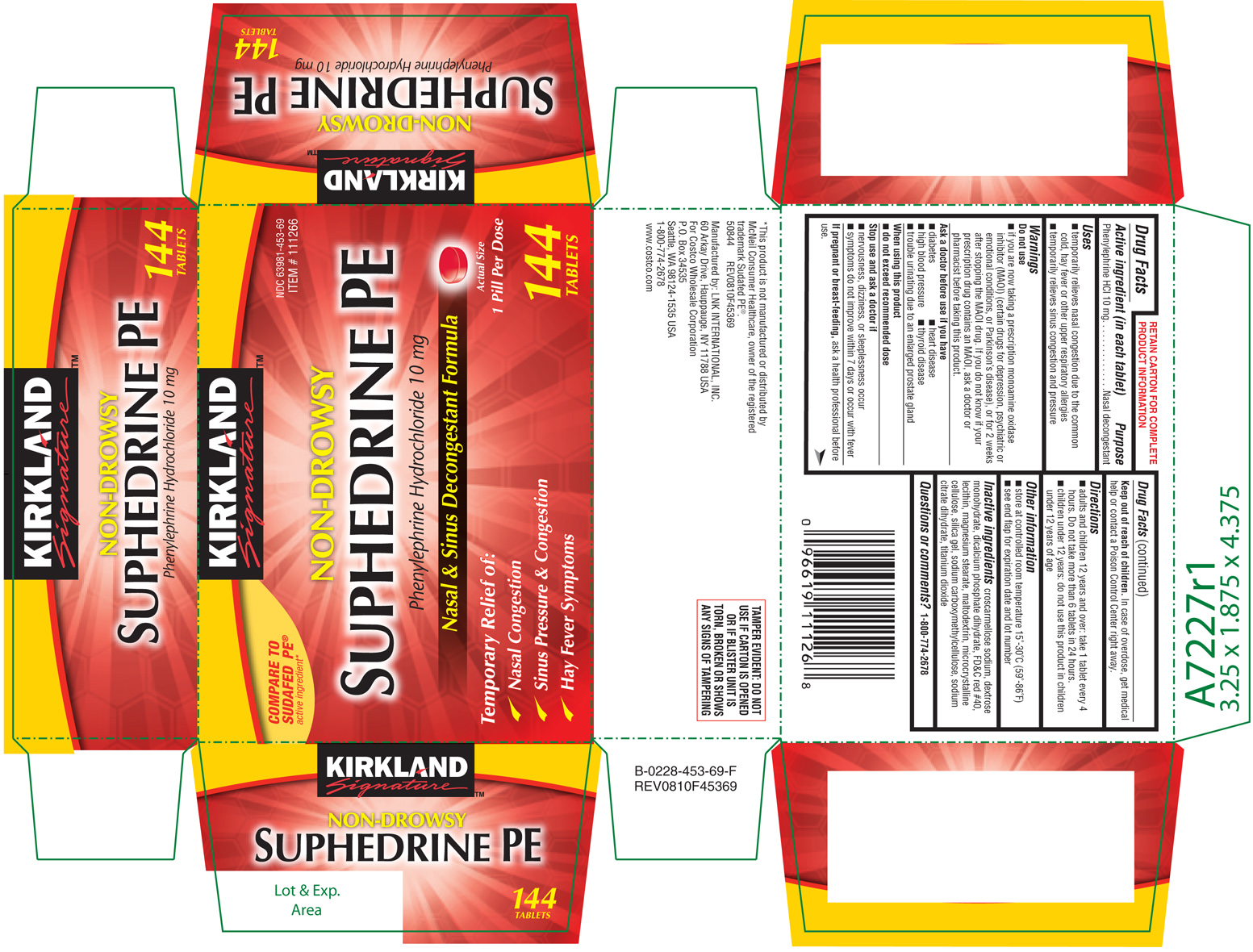 DRUG LABEL: Suphedrine PE 
NDC: 63981-453 | Form: TABLET, FILM COATED
Manufacturer: COSTCO WHOLESALE CORPORATION
Category: otc | Type: HUMAN OTC DRUG LABEL
Date: 20100921

ACTIVE INGREDIENTS: Phenylephrine Hydrochloride 10 mg/1 1
INACTIVE INGREDIENTS: Croscarmellose Sodium; Dextrose Monohydrate; Dibasic Calcium Phosphate Dihydrate; Fd&c Red No. 40; Magnesium Stearate; Maltodextrin; Cellulose, Microcrystalline; Silicon Dioxide; Carboxymethylcellulose Sodium; Trisodium Citrate Dihydrate

Active ingredient

(in each tablet)

Phenylephrine HCl 10 mg

Purpose

Nasal decongestant

Uses

- temporarily relieves nasal congestion due to the common cold, hay fever or other upper respiratory allergies
- temporarily relives sinus congestion and pressure

Do not use

if you are now taking a prescription monoamine oxidase inhibitor (MAOI) (certain drugs for depression, psychiatric or emotional conditions, or Parkinson's disease), or for 2 weeks after stopping the MAOI drug. If you do not know if your prescription drug contains an MAOI, ask a doctor or pharmacist before taking this product.

Ask a doctor before use if you have

- heart disease
- high blood pressure
- diabetes
- thyroid disease
- trouble urinating due to an enlarged prostate gland

When using this product

do not exceed the recommended dosage

Stop use and ask a doctor if

- nervousness, dizziness, or sleeplessness occur
- symptoms do not improve within 7 days or are accompanied by fever

If pregnant or breast-feeding,

ask a health professional before use.

Keep out of the reach of children.

In case of overdose, get medical help or contact a Poison Control Center right away.

Directions

- adults and children 12 years and over: 1 tablet every 4 hours. Do not take more than 6 tablets in 24 hours.
- children under 12 years: do not use this product in children under 12 years of age

Other information

- store at controlled room temperature 15°-30°C (59° to 86°F)
- see end flap for expiration date and lot number

Inactive ingredients

croscarmellose sodium, dextrose monohydrate, dicalcium phosphate dihydrate, FD&C red #40, lecithin, magnesium stearate, maltodextrin, microcrystalline cellulose, silica gel, sodium cardoxymethylcellulose, sodium citrate dihydrate, titanium dioxide

PRODUCT PACKAGING

The product packaging shown below represents a sample of that currently in use. Additional packaging may aslo be available.

KIRKLAND

Signature™

COMPARE TO

SUDAFED PE™

active ingredient*

NDC 63981-453-69

ITEM # 111266

NON-DROWSY

SUPHEDRINE PE

Phenylephrine Hydrochloride 10 mg

Nasal & Sinus Decongestant Formula

Temporary Relief of:

√ Nasal Congestion

√ Sinus Pressure & Congestion

√ Hay Fever Symptoms

Actual Size

1 Pill Per Dose

144

TABLETS

TAMPER EVIDENT: DO NOT USE IF CARTON IS OPENED OR IF BLISTER UNIT IS TORN, BROKEN OR SHOWS ANY SIGNS OF TAMPERING

50844 REV0810F45369

Manufactured by:

LNK INTERNATIONAL, INC.

60 Arkay Drive, Hauppauge, NY 11788 USA

For Costco Wholesale Corporation

P.O. Box 34535

Seattle, WA 98124-1535 USA

1-800-774-2678

www.cvs.com